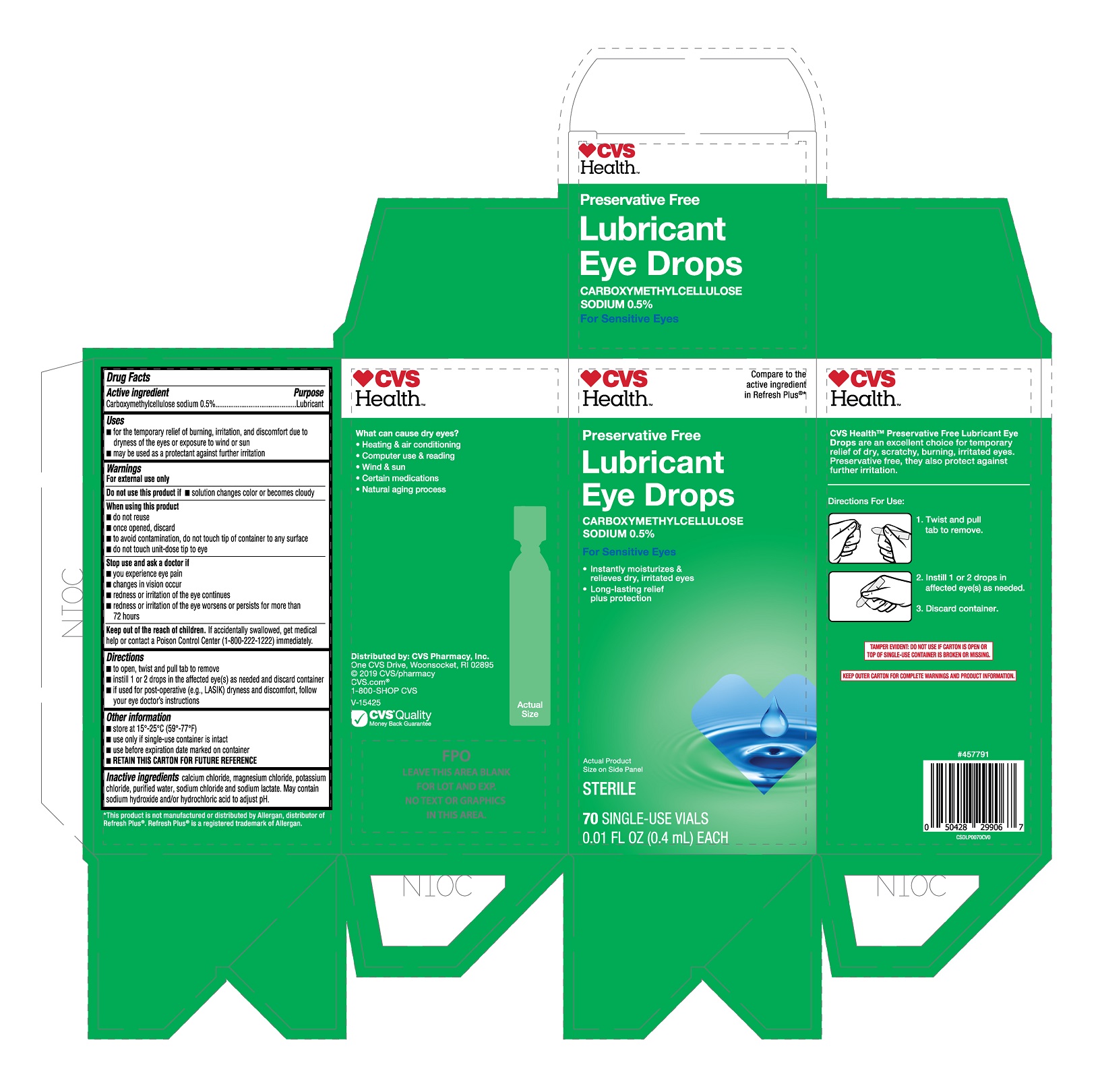 DRUG LABEL: CVS Lubricant Eye Drops
NDC: 69842-804 | Form: SOLUTION/ DROPS
Manufacturer: CVS Pharmacy, Inc.
Category: otc | Type: HUMAN OTC DRUG LABEL
Date: 20251230

ACTIVE INGREDIENTS: CARBOXYMETHYLCELLULOSE SODIUM 0.5 g/100 mL
INACTIVE INGREDIENTS: WATER; SODIUM CHLORIDE; SODIUM LACTATE; SODIUM HYDROXIDE; MAGNESIUM CHLORIDE; POTASSIUM CHLORIDE; HYDROCHLORIC ACID; CALCIUM CHLORIDE

CVS Lubricant Eye Drops 70ct (PLD)

Active ingredient

Carboxymethylcellulose sodium 0.5%

Purpose

Lubricant

Uses

- for the temporary relief of burning, irritation, and discomfort due to dryness of the eyes or exposure to wind or sun
- may be used as a protectant against further irritation

Warnings

For external use only

Do not use this product if

- solution changes color or becomes cloudy

When using this product

- do not reuse
- once opened, discard
- to avoid contamination, do not touch tip of container to any surface
- do not touch unit-dose tip to eye

Stop use and ask a doctor if

- you experience eye pain
- changes in vision occur
- redness or irritation of the eye continues
- redness or irritation of the eye worsens or persists for more than 72 hours

Keep out of the reach of children.

If accidentally swallowed, get medical help or contact a Poison Control Center (1-800-222-1222) immediately.

Directions

- to open, twist and pull tab to remove
- instill 1 or 2 drops in the affected eye(s) as needed and discard container
- if used for post-operative (e.g., LASIK) dryness and discomfort, follow your eye doctor's instructions

Other information

- store at 15°-25°C (59°-77°F)
- use only if single-use container is intact
- use before expiration date marked on container
- RETAIN THIS CARTON FOR FUTURE REFERENCE

Inactive ingredients

calcium chloride, magnesium chloride, potassium chloride, purified water, sodium chloride and sodium lactate. May contain sodium hydroxide and/or hydrochloric acid to adjust pH.